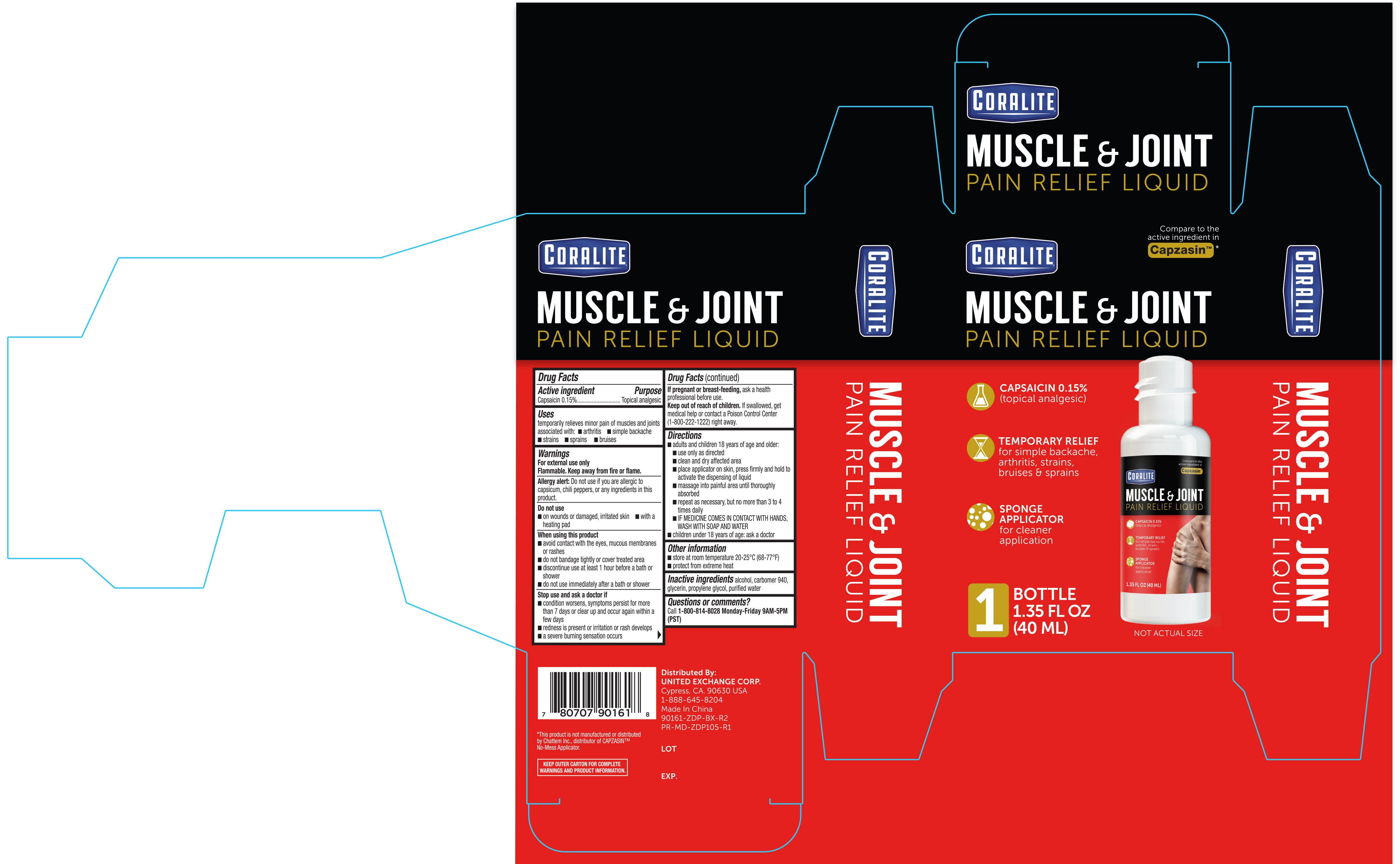 DRUG LABEL: Coralite Muscle and Joint Pain Relief
NDC: 65923-161 | Form: LIQUID
Manufacturer: United Exchange Corp.
Category: otc | Type: HUMAN OTC DRUG LABEL
Date: 20251021

ACTIVE INGREDIENTS: CAPSAICIN 0.0015 g/1 mL
INACTIVE INGREDIENTS: ALCOHOL; CARBOMER 940; GLYCERIN; PROPYLENE GLYCOL; WATER

Coralite Muscle & Joint Pain Relief Liquid 1.35 fl oz 90161

Active ingredient Purpose

Capsaicin 0.15%............................................................. Topical analgesic

Uses

temporarily relieves minor pain of muscles and joints associated with:

- arthritis
- simple backache
- strains
- sprains
- bruises

Warnings

For external use only

Flammable. Keep away from fire or flame.

Allergy alert: Do not use if you are allergic to capsicum, chili peppers, or any ingredients in this product.

Do not use

- on wounds or damaged, irritated skin
- with a heating pad

When using this product

- avoid contact with the eyes, mucous membranes or rashes
- do not bandage tightly or cover treated area
- discontinue use at least 1 hour before a bath or shower
- do not use immediately after a beath or shower

Stop use and ask a doctor if

- condition worsens, symptoms persist for more than 7 days or clear up and occur again within a few days
- redness is present or irritation or rash develops
- a severe burning sensation occurs

PREGNANCY OR BREAST FEEDING

If pregnant or breast-feeding ask a health professional before use.

Keep out of reach of children. If swallowed, get medical help or contact a Poison Control Center (1-800-222-1222) right away.

Directions

- adults and children 18 years of age and older:
- use only as directed
- clean and dry affected area
- place applicator on skin, press firmly and hold to activate the dispensing of liquid
- massage into painful area until thoroughly absorbed
- repeat as necessary, but no more than 3 to 4 times daily
- IF MEDICINE COMES IN CONTACT WITH HANDS, WASH WITH SOAP AND WATER
- children under 18 years of age: ask a doctor

Other information

- store at room temperature 20-25°C (68-77°F)
- protect from extreme heat

Inactive ingredients

alcohol, carbomer 940, glycerin, propylene glycol, purified water

DOSAGE AND ADMINISTRATION

Distributed by:

United Exchange Corp.

Cypress, CA 90630 USA

1-888-645-8204

Made in China